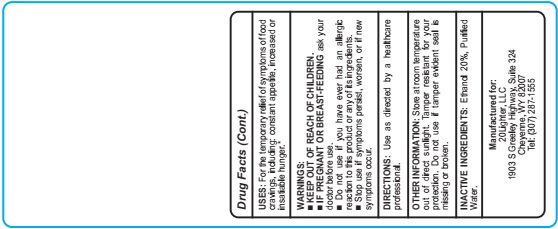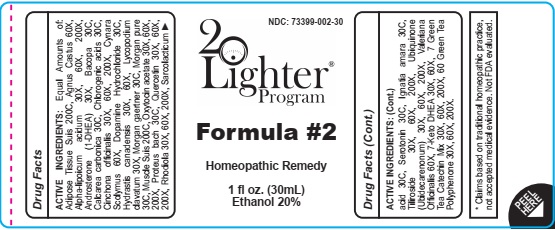 DRUG LABEL: Formula 2
NDC: 73399-002 | Form: LIQUID
Manufacturer: 20Lighter, LLC.
Category: homeopathic | Type: HUMAN OTC DRUG LABEL
Date: 20211115

ACTIVE INGREDIENTS: CHASTE TREE FRUIT 60 [hp_X]/30 mL; ALPHA LIPOIC ACID 30 [hp_X]/30 mL; ANDROSTERONE 30 [hp_X]/30 mL; OYSTER SHELL CALCIUM CARBONATE, CRUDE 30 [hp_C]/30 mL; CINCHONA OFFICINALIS BARK 30 [hp_X]/30 mL; CYNARA SCOLYMUS LEAF 60 [hp_X]/30 mL; GOLDENSEAL 30 [hp_X]/30 mL; LYCOPODIUM CLAVATUM SPORE 30 [hp_X]/30 mL; QUERCETIN 30 [hp_X]/30 mL; LACTIC ACID, L- 30 [hp_C]/30 mL; SEROTONIN 30 [hp_C]/30 mL; STRYCHNOS IGNATII SEED 30 [hp_C]/30 mL; TILIROSIDE 30 [hp_X]/30 mL; UBIDECARENONE 30 [hp_X]/30 mL; VALERIAN 60 [hp_X]/30 mL
INACTIVE INGREDIENTS: ALCOHOL; Water

Formula 2

ACTIVE INGREDIENT

ACTIVE INGREDIENTS: Equal Amounts of: Adipose Tissue Suis 200C, Agnus Castus 60X, Alpha-lipoicum acidum 30X, 60X, 200X, Androsterone (1-DHEA) 30X, Bacopa 30C, Calcarea carbonica 30C, Chlorogenic acids 30C, Cinchona officinalis 30X, 60X, 200X, Cynara Scolymus 60X, Dopamine Hydrochloride 30C, Hydrastis canadensis 30X, 60X, Lycopodium clavatum 30X, Morgan gaertner 30C, Morgan pure 30C, Muscle Suis 200C, Oxytocin acetate 30X, 60X, 200X, Proteus bach 30C, Quercetin 30X, 60X, 200X, Rhodiola 30X, 60X, 200X, Sarcolacticum

* Claims based on traditional homeopathic practice, not accepted medical evidence. Not FDA evaluated.

INDICATIONS AND USAGE

USES: For the temporary relief of symptoms of food cravings, including: constant appetite, increased or insatiable hunger.*

▀ KEEP OUT OF REACH OF CHILDREN.
▀ IF PREGNANT OR BREAST-FEEDING ask your doctor before use.
▀ Do not use if you have ever had an allergic reaction to this product or any of its ingredients.
▀ Stop use if symptoms persist, worsen, or if new symptoms occur.

▀ KEEP OUT OF REACH OF CHILDREN.

DOSAGE AND ADMINISTRATION

DIRECTIONS: Use as directed by a healthcare professional.

INACTIVE INGREDIENTS: Ethanol 20%, Purified Water

QUESTIONS

Manufactured for:
20Lighter, LLC
1903 S Greeley Highway, Suite 324
Cheyenne, WY 82007
Tel: (307) 287-1555

PACKAGE LABEL

73399-002-30

20Lighter Program

Formula #2

Homeopathic Remedy

1 fl oz. (30mL)

Ethanol 20%

PURPOSE

USES: For the temporary relief of symptoms of food cravings, including: constant appetite, increased or insatiable hunger.*